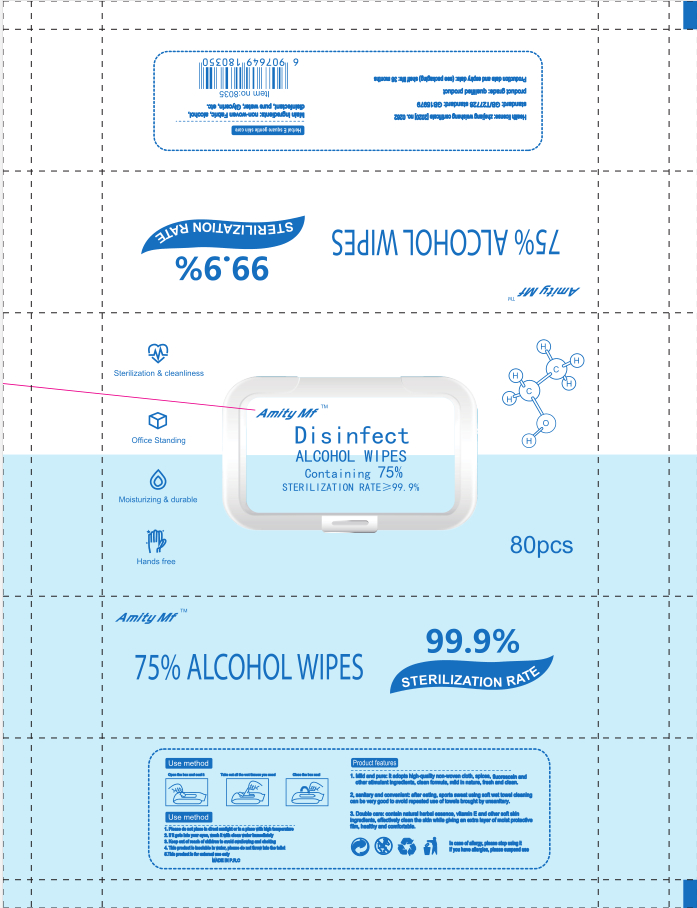 DRUG LABEL: AICOHOI  Wipes
NDC: 96387-001 | Form: CLOTH
Manufacturer: Yiwu Aimili Maternal And Child Supplies Co.,Ltd
Category: otc | Type: HUMAN OTC DRUG LABEL
Date: 20200728

ACTIVE INGREDIENTS: ALCOHOL 261.75 g/80 1
INACTIVE INGREDIENTS: WATER

DOSAGE AND ADMINISTRATION

Please do not place in dlrect sunlight or in a place with high temperature

INACTIVE INGREDIENT

Water

INDICATIONS AND USAGE

1.Open the box and seal It
2. Take out all the wet tlssues you need
3.Close the box seal

ACTIVE INGREDIENT

Ethyl Alcohol

keep out of reach of children

PURPOSE

Disinfection
Sterilization
No Rinseing

WARNINGS

1. Please do not place in dlrect sunlight or in a place with high temperature
2. Ifit gets into your eyes, wash it with dlean water immediately
3. Keep out of reach of children to avoid swallowing and choking
4. This product is insoluble in water, please do not throw into the tillet
5.This product is for extermal use only